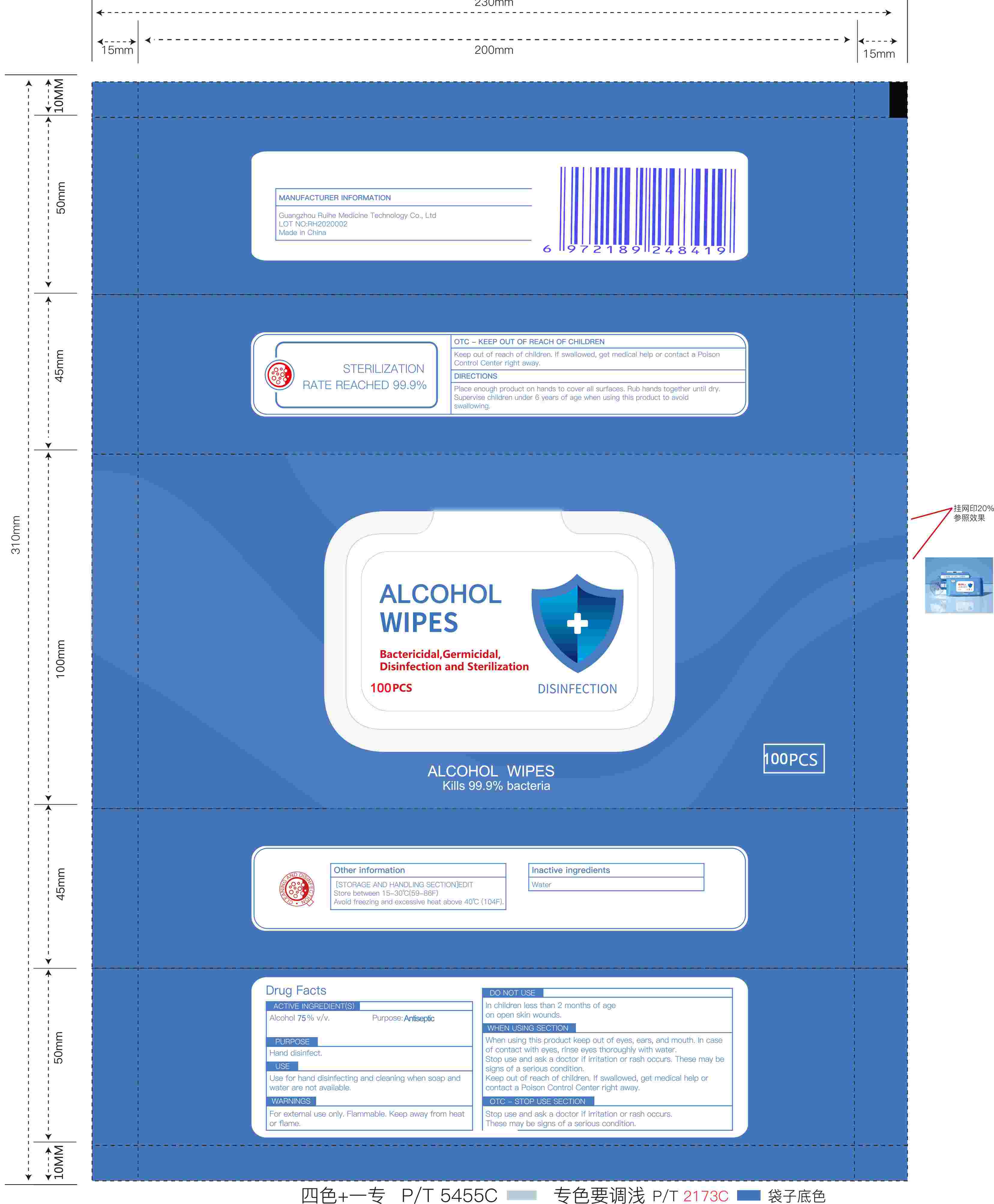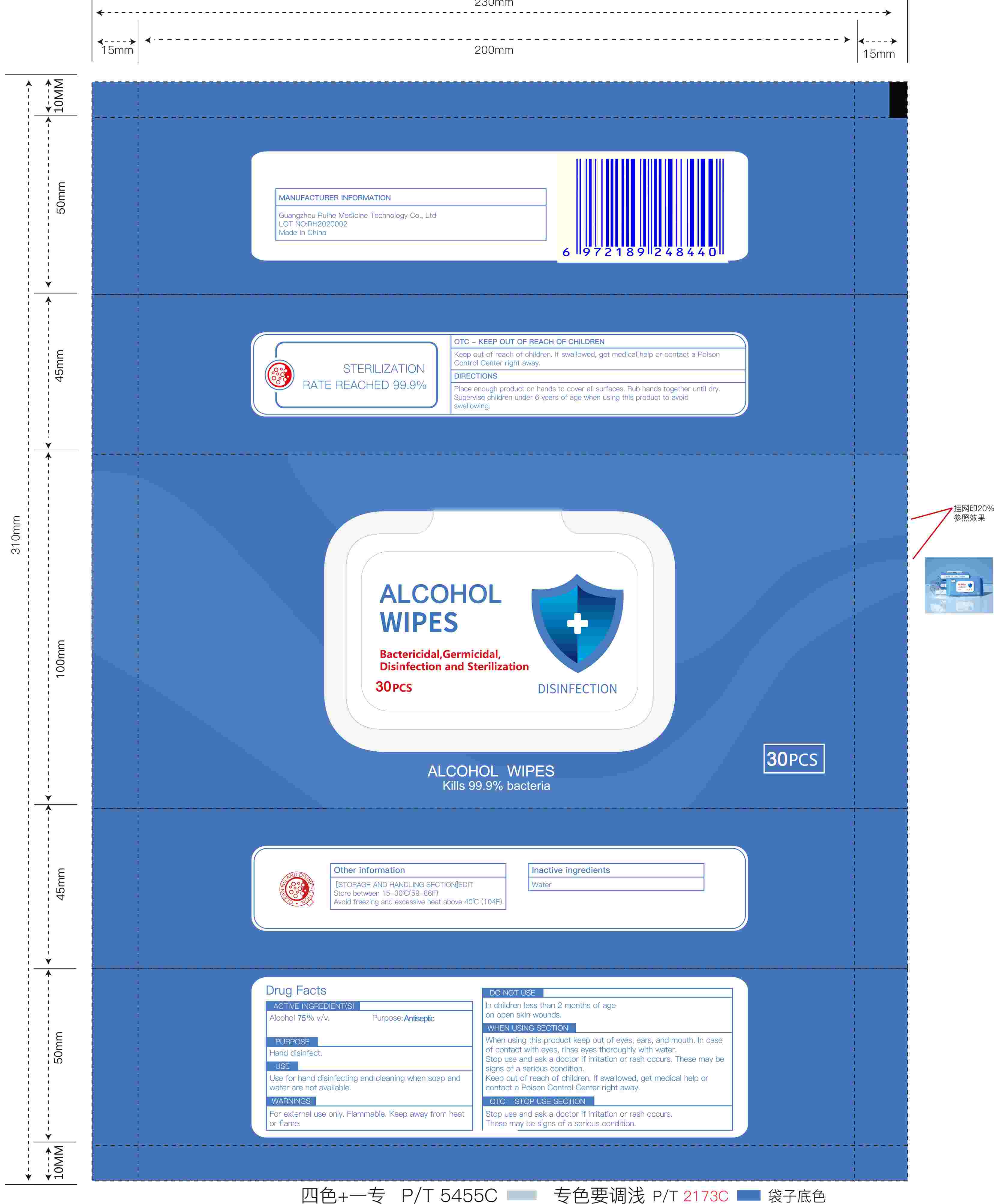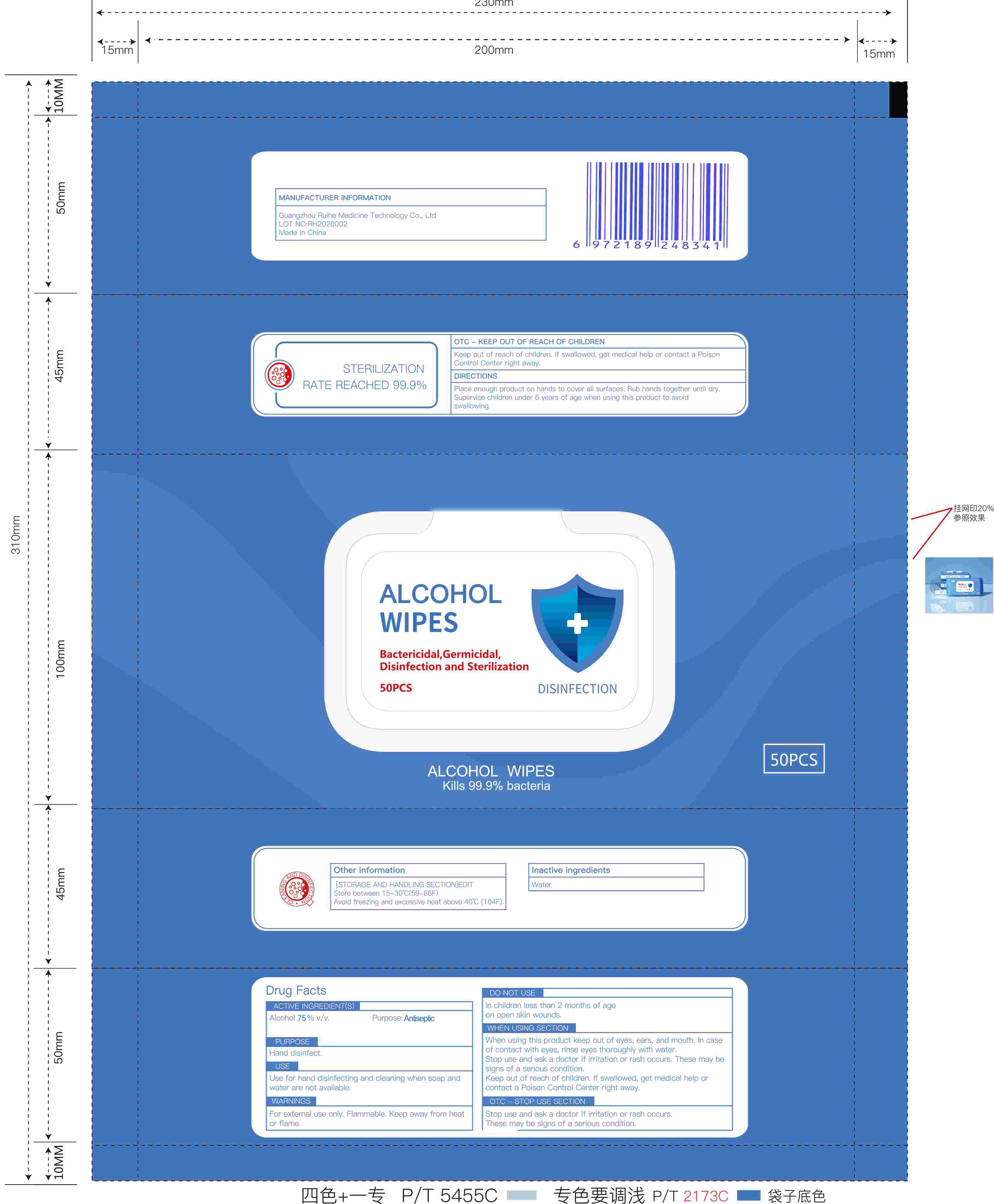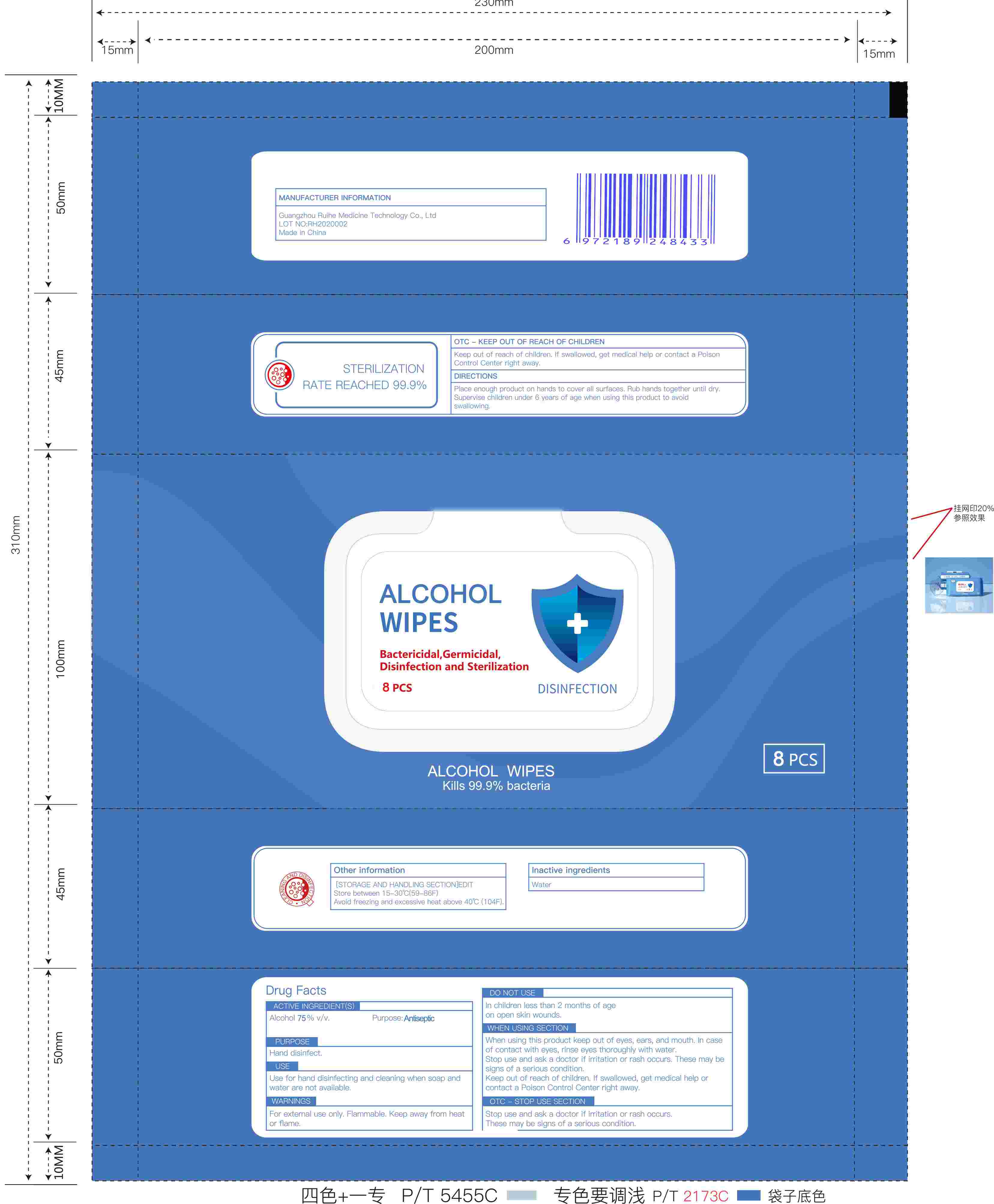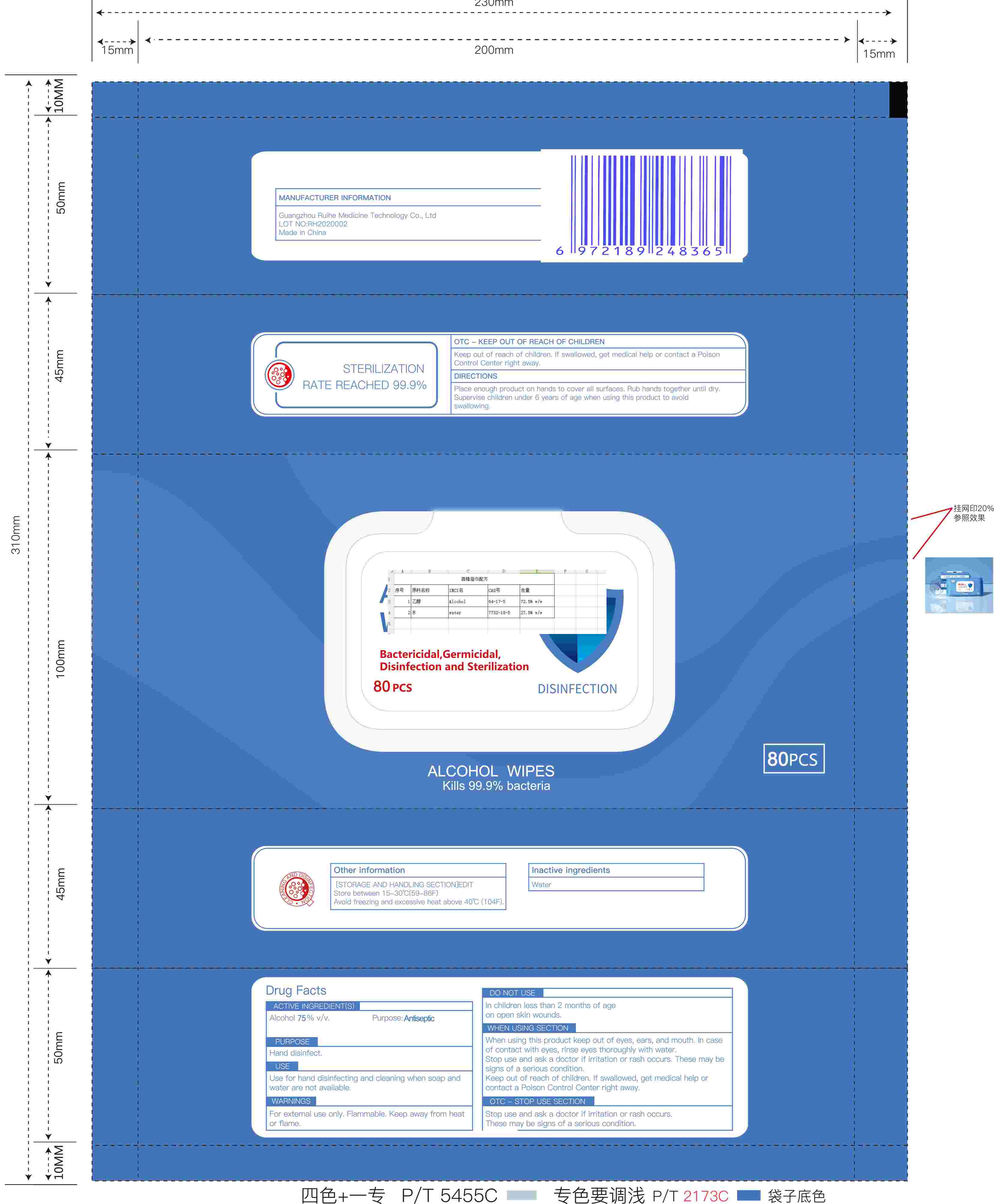 DRUG LABEL: ALCOHOL WIPES
NDC: 78293-007 | Form: CLOTH
Manufacturer: Guangdong Bolicen Bio-Technology Co., Ltd.
Category: otc | Type: HUMAN OTC DRUG LABEL
Date: 20200630

ACTIVE INGREDIENTS: ALCOHOL 75 1/100 1
INACTIVE INGREDIENTS: WATER

ALCOHOL WIPES

Active Ingredient(s)

Alcohol75%v/v

Purpose

Antiseptic
Hand disinfect

Use

Use for hand disinfecting and cleaning when soap and water are not availableI.

Warnings

For external use only. Flammable. Keep away from heat or flame.

Do not use

In children less than 2 months of age
on open skin wounds

When using this product keep out of eyes, ears, and mouth. In case of contact with eyes, rinse eyes thoroughly with water.
Stop use and ask a doctor if irritation or rash occurs. These may be signs of a serious condition.
Keep out of reach of children. If swallowed, get medical help or contact a Poison Control Center right away

Stop use and ask a doctor if irritation or rash occurs. These may be signs of a serious condition.

Keep out of reach of children. If swallowed, get medical help or contact a Poison Control Center right away

Directions

Place enough product on hands to cover all surfaces. Rub hands together until dry.
Supervise children under 6 years of age when using this product to avoid swallowing.

Other information

STORAGE AND HANDLING SECTION
Store between 15-30°C(59-86F).
Avoid freezing and excessive heat above 40°C(104F).

Inactive ingredients

Water